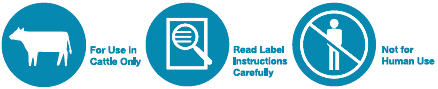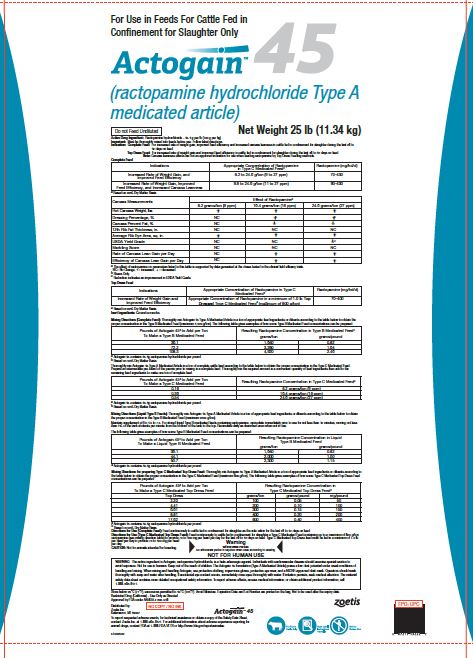 DRUG LABEL: Actogain
NDC: 54771-8728 | Form: POWDER
Manufacturer: Zoetis Inc.
Category: animal | Type: OTC TYPE A MEDICATED ARTICLE ANIMAL DRUG LABEL
Date: 20231212

ACTIVE INGREDIENTS: RACTOPAMINE HYDROCHLORIDE 100 g/1 kg
INACTIVE INGREDIENTS: WATER; SOYBEAN OIL

Actogain™ 45

Actogain™ 45

(ractopamine hydrochloride Type A medicated article)

For Use in Feeds For Cattle Fed in Confinement for Slaughter Only

Net Weight 25 lb (11.34kg)

Do not Feed Undiluted

DESCRIPTION

Active Drug Ingredient:Ractopamine hydrochloride – 45.4 g per lb (100 g per kg)
Important:Must be thoroughly mixed into feeds before use. Follow label directions.
Indication: Complete Feed: | For increased rate of weight gain, improved feed efficiency and increased carcass leanness in cattle fed in confinement for slaughter during the last 28 to 42 days on feed.
Top Dress Feed: | For increased rate of weight gain and improved feed efficiency in cattle fed in confinement for slaughter during the last 28 to 42 days on feed.
Note: | Carcass leanness effects are not an approved indication for use when feeding ractopamine by Top Dress Feeding methods.

Complete Feed

Indications | Appropriate Concentration of Ractopamine in Type C Medicated Feed [Based on 90% Dry Matter Basis] | Ractopamine (mg/hd/d)
Increased Rate of Weight Gain, and Improved Feed Efficiency | 8.2 to 24.6 g/ton (9 to 27 ppm) | 70-430
Increased Rate of Weight Gain, Improved Feed Efficiency, and Increased Carcass Leanness | 9.8 to 24.6 g/ton (11 to 27 ppm) | 90-430

Carcass Measurements | Effect of Ractopaminea
Carcass Measurements | 8.2 grams/ton (9 ppm) | 16.4 grams/ton (18 ppm) | 24.6 grams/ton (27 ppm)
Hot Carcass Weight, lbs | ↑ | ↑ | ↑
Dressing Percentage, % | NC | ↑b | ↑b
Carcass Percent Fat, % | NC | ↓ | ↓
12th Rib Fat Thickness, in. | NC | NC | NC
Average Rib Eye Area, sq. in. | ↑ | ↑ | ↑
USDA Yield Grade | NC | NC | ↓c
Marbling Score | NC | NC | NC
Rate of Carcass Lean Gain per Day | NC | ↑ | ↑
Efficiency of Carcass Lean Gain per Day | NC | ↑ | ↑
a The effect of ractopamine on parameters listed in this table is supported by data generated at the doses tested in the clinical field efficacy trials.
NC= No Change, ↑= increased, ↓ = decreased
b Steers Only
c Reduction indicates an improvement in USDA Yield Grade.

Top Dress Feed

Indications | Appropriate Concentration of Ractopamine in Type C Medicated Feeda | Ractopamine (mg/hd/d)
Increased Rate of Weight Gain and Improved Feed Efficiency | Appropriate Concentration of Ractopamine in a minimum of 1.0 lb Top Dressed Type C Medicated Feeda (maximum of 800 g/ton) | 70-400

aBased on 90% Dry Matter Basis

Inert Ingredients: Ground corncobs.

Mixing Directions (Complete Feed)

Thoroughly mix Actogain 45 Type A Medicated Article in a ton of appropriate feed ingredients or diluents according to the table below to obtain the proper concentration in the Type B Medicated Feed (maximum 4,920 g/ton). The following table gives examples of how some Type B Medicated Feed concentrations can be prepared:

Pounds of Actogain 45a to Add per Ton To Make a Type B Medicated Feed | Resulting Ractopamine Concentration in Type B Medicated Feedb
Pounds of Actogain 45a to Add per Ton To Make a Type B Medicated Feed | grams/ton | grams/pound
36.1 | 1,640 | 0.82
72.2 | 3,280 | 1.64
108.3 | 4,920 | 2.46

a Actogain 45 contains 45.4g ractopamine hydrochloride per pound
b Based on 90% Dry Matter Basis

Thoroughly mix Actogain 45 Type A Medicated Article in a ton of complete cattle feed according to the table below to obtain the proper concentration in the Type C Medicated Feed. Prepare an intermediate pre-blend of the premix prior to mixing in a complete feed. Thoroughly mix the required amount in a convenient quantity of feed ingredients then add to the remaining feed ingredients to make one ton of complete feed.

Pounds of Actogain 45a to Add per Ton To Make a Type C Medicated Feed | Resulting Ractopamine Concentration in Type C Medicated Feedb
0.18 | 8.2 grams/ton (9 ppm)
0.36 | 16.4 grams/ton (18 ppm)
0.54 | 24.6 grams/ton (27 ppm)

a Actogain 45 contains 45.4g ractopamine hydrochloride per pound
b Based on 90% Dry Matter Basis

Mixing Directions (Liquid Type B Feeds)

Thoroughly mix Actogain 45 Type A Medicated Article in a ton of appropriate feed ingredients or diluents according to the table below to obtain the proper concentration in the Type B Medicated Feed (maximum 2300 g/ton).

Maintain supplement pH to 4.5 to 7.5. For stored liquid Type B medicated feeds containing ractopamine, recirculate immediately prior to use for not less than 10 minutes, moving not less than 1% of the tank contents per minute from the bottom of the tank to the top. Recirculate daily as described even when not in use.

The following table gives examples of how some Type B Medicated Feed concentrations can be prepared:

Pounds of Actogain 45a to Add per Ton To Make a Liquid Type B Medicated Feed | Resulting Ractopamine Concentration in Liquid Type B Medicated Feed
Pounds of Actogain 45a to Add per Ton To Make a Liquid Type B Medicated Feed | grams/ton | grams/pound
36.1 | 1,640 | 0.82
44.1 | 2,000 | 1.00
50.7 | 2,300 | 1.15

a Actogain 45 contains 45.4g ractopamine hydrochloride per pound

Mixing Directions for preparing Type C Medicated Top Dress Feed

Thoroughly mix Actogain 45 Type A Medicated Article in a ton of appropriate feed ingredients or diluents according to the table below to obtain the proper concentration in the Type C Medicated Feed (maximum 800 g/ton). The following table gives examples of how some Type C Medicated Top Dress Feed concentrations can be prepared:

Pounds of Actogain 45a to Add per Ton To Make a Type C Medicated Top Dress Feed | Resulting Ractopamine Concentration in Type C Medicated Top Dress Feedb
Top Dress | grams/ton | grams/pound | mg/pound
2.20 | 100 | 0.05 | 50
4.41 | 200 | 0.10 | 100
6.61 | 300 | 0.15 | 150
8.81 | 400 | 0.20 | 200
17.62 | 800 | 0.40 | 400

a Actogain 45 contains 45.4g ractopamine hydrochloride per pound

b Based on 90% Dry Matter Basis

DOSAGE AND ADMINISTRATION

Directions for Use (Complete Feed): Feed continuously to cattle fed in confinement for slaughter as the sole ration for the last 28 to 42 days on feed.

Directions for Use (Type C Medicated Top Dress Feed): Feed continuously to cattle fed in confinement for slaughter a Type C Medicated Feed containing up to a maximum of 800 g/ton ractopamine (see mixing direction table) to provide 70 to 400 mg per head per day for the last 28 to 42 days on feed. Type C Medicated Top Dress feed must be fed in a minimum of 1.0 lb per head per day to provide 70 to 400 mg per head per day.

CAUTION

Not for animals intended for breeding.

NOT FOR HUMAN USE

Withdrawal Period:
No withdrawal period is required when used according to labeling.

WARNING

WARNING: The active ingredient in Actogain, ractopamine hydrochloride, is a beta-adrenergic agonist. Individuals with cardiovascular disease should exercise special caution to avoid exposure. Not for use in humans. Keep out of the reach of children. The Actogain 45 formulation (Type A Medicated Article) poses a low dust potential under usual conditions of handling and mixing. When mixing and handling Actogain, use protective clothing, impervious gloves, protective eye wear, and a NIOSH-approved dust mask. Operators should wash thoroughly with soap and water after handling. If accidental eye contact occurs, immediately rinse eyes thoroughly with water. If irritation persists, seek medical attention. The material safety data sheet contains more detailed occupational safety information. To report adverse effects, access medical information, or obtain additional product information, call 1-888-963-8471.

STORAGE AND HANDLING

Store below 25ºC (77ºF), excursions permitted to 40ºC (104ºF). Avoid Moisture. Expiration Date and Lot Number are printed on the bag. Not to be used after the expiry date.
Restricted Drug (California) – Use Only as Directed
Approved by FDA under ANADA # 200-548

Distributed by:
Zoetis Inc.
Kalamazoo, MI 49007

ADVERSE REACTIONS

To report suspected adverse events, for technical assistance or obtain a copy of the Safety Data Sheet, contact Zoetis Inc. at 1-888-963-8471. For additional information about adverse experience reporting for animal drugs, contact FDA at 1-888-FDA-VETS or http://www.fda.gov/reportanimalae.

51032502

PRINCIPAL DISPLAY PANEL - 11.34 kg Bag

51032502